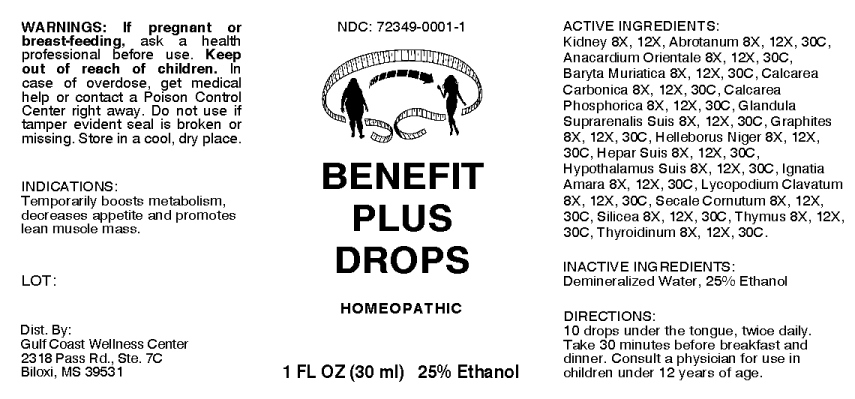 DRUG LABEL: Benefit Plus Drops
NDC: 72349-0001 | Form: LIQUID
Manufacturer: Gulf Coast Wellness Center
Category: homeopathic | Type: HUMAN OTC DRUG LABEL
Date: 20180817

ACTIVE INGREDIENTS: PORK KIDNEY 8 [hp_X]/1 mL; ARTEMISIA ABROTANUM FLOWERING TOP 8 [hp_X]/1 mL; SEMECARPUS ANACARDIUM JUICE 8 [hp_X]/1 mL; BARIUM CHLORIDE DIHYDRATE 8 [hp_X]/1 mL; OYSTER SHELL CALCIUM CARBONATE, CRUDE 8 [hp_X]/1 mL; TRIBASIC CALCIUM PHOSPHATE 8 [hp_X]/1 mL; SUS SCROFA ADRENAL GLAND 8 [hp_X]/1 mL; GRAPHITE 8 [hp_X]/1 mL; HELLEBORUS NIGER ROOT 8 [hp_X]/1 mL; PORK LIVER 8 [hp_X]/1 mL; SUS SCROFA HYPOTHALAMUS 8 [hp_X]/1 mL; STRYCHNOS IGNATII SEED 8 [hp_X]/1 mL; LYCOPODIUM CLAVATUM SPORE 8 [hp_X]/1 mL; CLAVICEPS PURPUREA SCLEROTIUM 8 [hp_X]/1 mL; SILICON DIOXIDE 8 [hp_X]/1 mL; SUS SCROFA THYMUS 8 [hp_X]/1 mL; THYROID, PORCINE 8 [hp_X]/1 mL
INACTIVE INGREDIENTS: WATER; ALCOHOL

Drug Facts:

ACTIVE INGREDIENTS:

Kidney (Suis) 8X, 12X, Abrotanum 8X, 12X, 30C, Anacardium Orientale 8X, 12X, 30C, Baryta Muriatica 8X, 12X, 30C, Calcarea Carbonica 8X, 12X, 30C, Calcarea Phosphorica 8X, 12X, 30C, Glandula Suprarenalis Suis 8X, 12X, 30C, Graphites 8X, 12X, 30C, Helleborus Niger 8X, 12X, 30C, Hepar Suis 8X, 12X, 30C, Hypothalamus Suis 8X, 12X, 30C, Ignatia Amara 8X, 12X, 30C, Lycopodium Clavatum 8X, 12X, 30C, Secale Cornutum 8X, 12X, 30C, Silicea 8X, 12X, 30C, Thymus (Suis) 8X, 12X, 30C, Thyroidinum (Suis) 8X, 12X, 30C.

INDICATIONS:

Temporarily boosts metabolism, decreases appetite and promotes lean muscle mass.

WARNINGS:

If pregnant or breast-feeding, ask a health professional before use.

Keep out of reach of children. In case of overdose, contact a physician or Poison Control Center right away.

Do not use if tamper evident seal is broken or missing.

Store in a cool, dry place.

Keep out of reach of children. In case of overdose, contact a physician or Poison Control Center right away.

DIRECTIONS:

10 drops under the tongue, twice daily. Take 30 minutes before breakfast and dinner. Consult a physician for use in children under 12 years of age.

INDICATIONS:

Temporarily boosts metabolism, decreases appetite and promotes lean muscle mass.

INACTIVE INGREDIENTS:

Demineralized Water, 25% Ethanol

QUESTIONS:

Dist. By:

Gulf Coast Wellness Center

2318 Pass Rd., Ste. 7C

Biloxi, MS 39531

PACKAGE LABEL DISPLAY:

NDC: 72349-0001-1

BENEFIT

PLUS

DROPS

HOMEOPATHIC

1 FL OZ (30 ml)